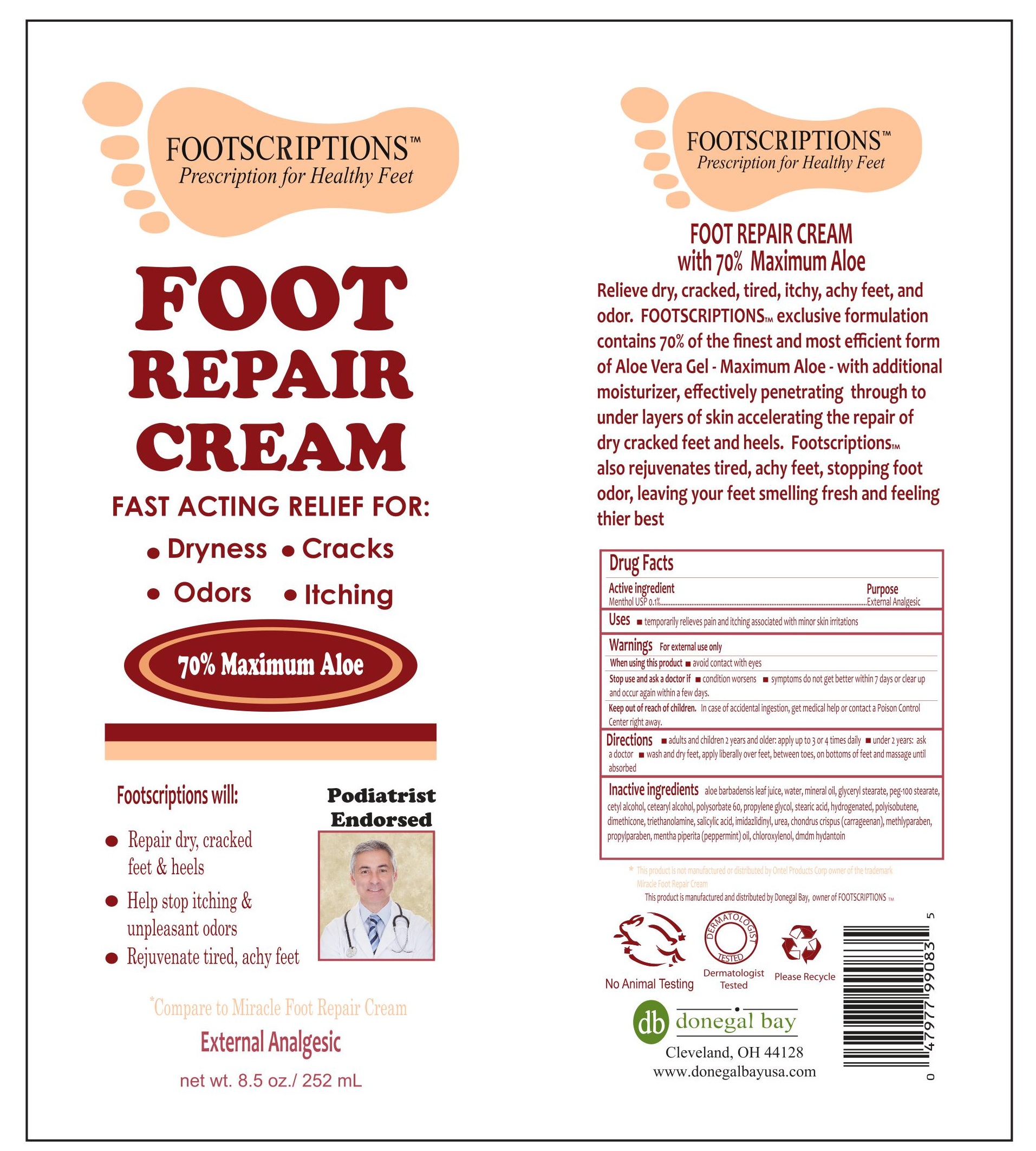 DRUG LABEL: Footscriptions Foot Repair
NDC: 70990-002 | Form: CREAM
Manufacturer: Donegal Bay Ltd
Category: otc | Type: HUMAN OTC DRUG LABEL
Date: 20161012

ACTIVE INGREDIENTS: MENTHOL 0.1 g/100 mL
INACTIVE INGREDIENTS: WATER; ALOE ANDONGENSIS LEAF; CETYL ALCOHOL; MINERAL OIL; GLYCERYL STEARATE SE; PEG-100 STEARATE; POLYSORBATE 60; PROPYLENE GLYCOL; STEARIC ACID; HYDROGENATED POLYBUTENE (1300 MW); DIMETHICONE; SALICYLIC ACID; UREA; CHONDRUS CRISPUS; METHYLPARABEN; PROPYLPARABEN; PEPPERMINT OIL; CHLOROXYLENOL; DMDM HYDANTOIN

Daily Moisturizing Lotion

Active Ingredient:

Menthol USP 0.1%

Purpose:

External Analgesic

Uses:

Temporarily relieves pain and itching associated with skin irritations

Warnings:

For external use only

When using this product, avoid contacting with eyes

Stop use and ask a doctor if condition worsens or if symptoms last for more than 7 days or clear up and occur again within a few days

Keep out of reach of children. In case of accidental ingestion, get medical help or contact a Poison Control Center right away.

DOSAGE AND ADMINISTRATION

Direction:

Adults and children 2 years and older: apply up to 3-4 times daily.

Under 2 years: ask a doctor

Wash and dry feet, apply liberally over feet, between toes, on bottoms of feet, and message until absorbed.

Inactive Ingredients:

Aloe Barbadenis Leaf Juice, Water, Mineral Oil, Glycerryl Stearate, PEG-100 Stearate, Cetyl Alcohol, Cetearyl Alcohol, Polysorbate 60, Propylene Glycol, Stearic Acid, Hydrogenated Polyisobutene, Dimethicone, Triethanolamine, Salicylic Acid, Imidazlidinyl, Urea, Chondrus Crispus, Methylparaben, Propylparaben, Mentha Piperita (peppermint) Oil, Chloroxylenol, DMDM Hydantoin